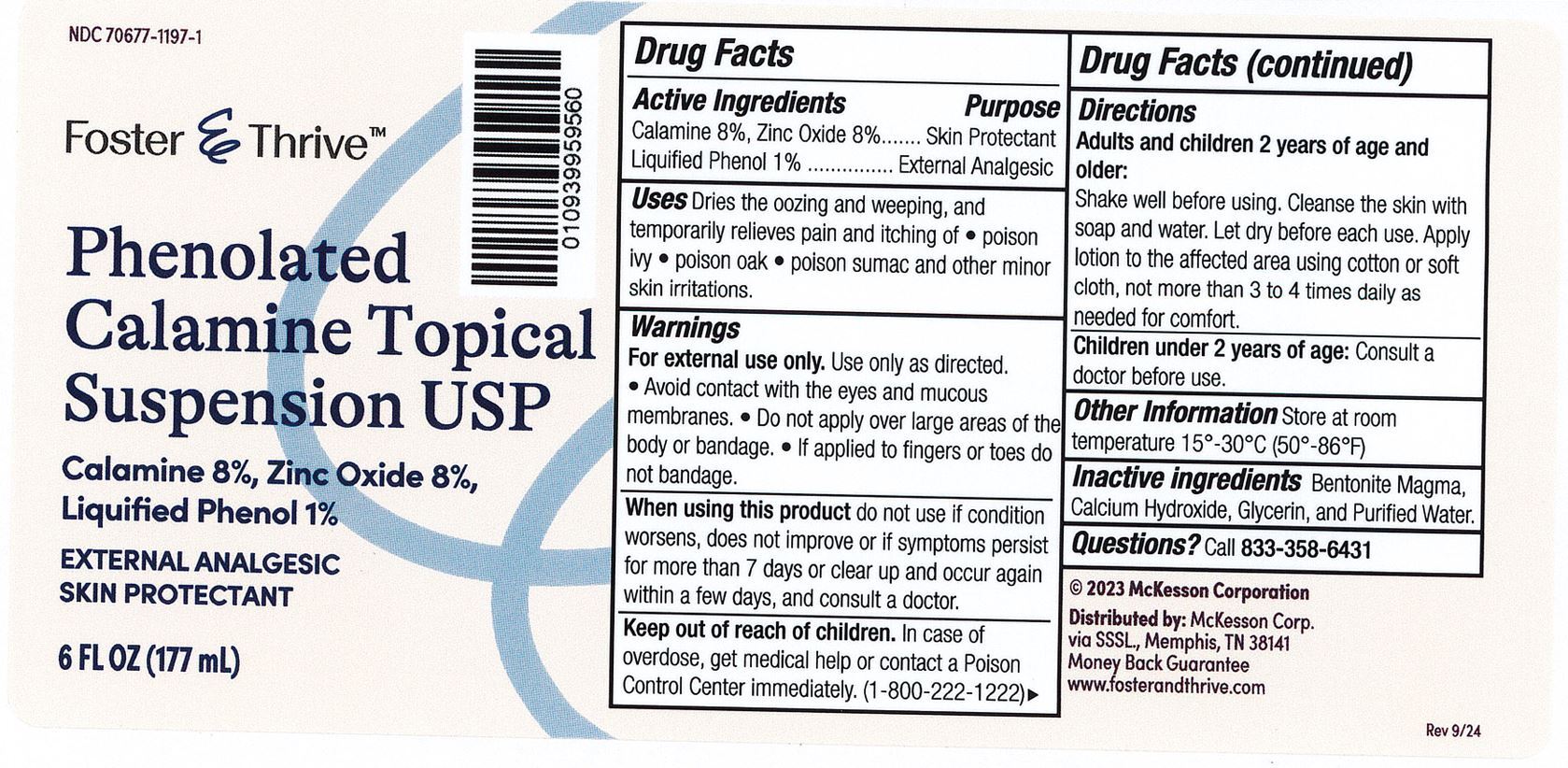 DRUG LABEL: Foster and Thrive Phenolated Calamine
NDC: 70677-1197 | Form: LOTION
Manufacturer: Strategic Sourcing Services LLC
Category: otc | Type: HUMAN OTC DRUG LABEL
Date: 20241217

ACTIVE INGREDIENTS: ZINC OXIDE 160 mg/1 mL; PHENOL 10 mg/1 mL
INACTIVE INGREDIENTS: BENTONITE; CALCIUM HYDROXIDE; GLYCERIN; WATER

Foster & Thrive Phenolated Calamine Lotion USP

Drug Facts

Active Ingredient

Calamine 8%

Purpose

Skin Protectant

Active Ingredient

Zinc Oxide 8%

Purpose

Skin Protectant

Active Ingredient

Liquefied Phenol

Purpose

Topical Analgesic

Uses

Dries the oozing and weeping and temporarily pain and itching of poison ivy, poison oak, and poison sumac, or other minor skin irritations

Warnings

- For external use only. Use only as directed.
- Avoid contact with eyes and mucous membranes.
- Do not apply to large areas of the body or in large quantities, particularly over raw or blistered areas.
- If applied to fingers or toes do not bandage.

Ask a doctor

before using on children under 2 years of age.

When using this product. Discontinue use if condition worsen or does not improve within 7 days and consult a doctor.

Keep out of reach of children.

In case of accidental ingestion, seek professional assistance or contact a poison Control Center immediately.

directions (Shake well before using)

Adult and children 2 years of age and older: Shake well before using. Cleanse the skin with soap and water and let dry before each use. Apply product to the affected area using cotton or soft cloth, not more than 3 to 4 times daily as needed for comfort.

Children under 2 years of age: Consult a doctor before use.

Other Information.

Store at room temperature 15-30C (59-86F)

Inactive Ingredients.

Bentonite Magma, Calcium Hydroxide, Glycerin, Purified Water.